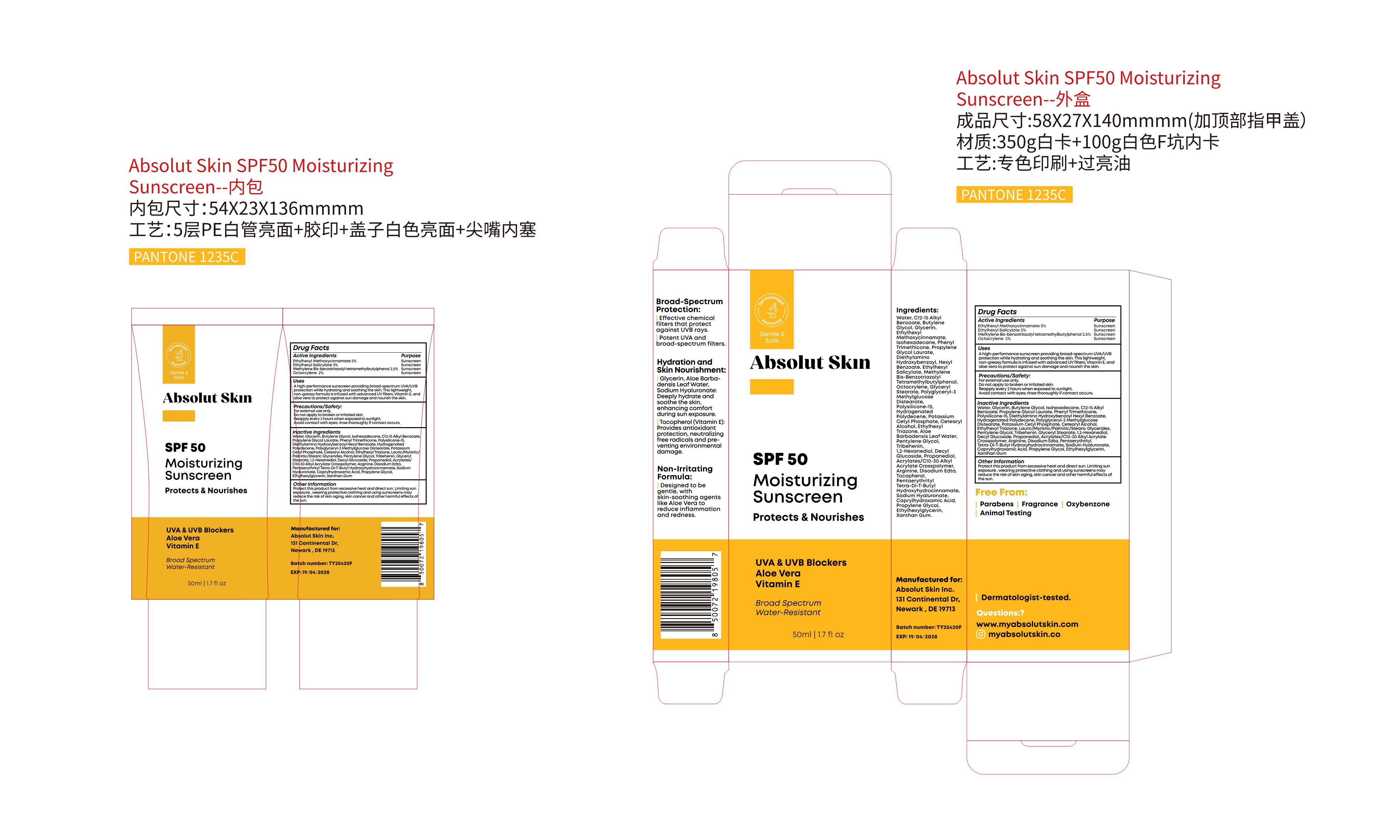 DRUG LABEL: Absolut Skin SPF 50 Moisturizing Sunscreen
NDC: 84066-105 | Form: CREAM
Manufacturer: Guangzhou Tata Biotechnology Co., Ltd.
Category: otc | Type: HUMAN OTC DRUG LABEL
Date: 20251222

ACTIVE INGREDIENTS: METHYLENE BIS-BENZOTRIAZOLYL TETRAMETHYLBUTYLPHENOL 2.5 mg/100 mL; OCTOCRYLENE 2 mg/100 mL; ETHYLHEXYL METHOXYCINNAMATE 5 mg/100 mL; ETHYLHEXYL SALICYLATE 3 mg/100 mL
INACTIVE INGREDIENTS: PENTAERYTHRITYL TETRA-DI-T-BUTYL HYDROXYHYDROCINNAMATE; PHENYL TRIMETHICONE; PROPYLENE GLYCOL; CAPRYLHYDROXAMIC ACID; C14-18 MONO-AND DI-GLYCERIDES; PENTYLENE GLYCOL; XANTHAN GUM; WATER; BUTYLENE GLYCOL; ISOHEXADECANE; C12-15 ALKYL BENZOATE; CETEARYL ALCOHOL; GLYCERYL STEARATE; 1,2-HEXANEDIOL; DIETHYLAMINO HYDROXYBENZOYL HEXYL BENZOATE; POLYSILICONE-15; POLYGLYCERYL-3 METHYLGLUCOSE DISTEARATE; DECYL GLUCOSIDE; GLYCERIN; POTASSIUM CETYL PHOSPHATE; ETHYLHEXYL TRIAZONE; ETHYLHEXYLGLYCERIN; ACRYLATES/C10-30 ALKYL ACRYLATE CROSSPOLYMER (60000 MPA.S); EDETATE DISODIUM; SODIUM HYALURONATE; PROPYLENE GLYCOL LAURATE; HYDROGENATED POLYDECENE (1500 CST); PROPANEDIOL; ARGININE; TRIBEHENIN

ACTIVE INGREDIENT

Ethylhexyl Methoxycinnamate 5%

Ethylhexyl Salicylate 3%

Methylene Bis-benzotriazolyl tetramethylbutyiphenol 2.5%

Octocrylene 2%

PURPOSE

Sunscreen

INDICATIONS AND USAGE

Ahigh-performance sunscreen providing broad-spectrum UVA/UVBprotection while hydrating and soothing the skin.

This lightweight,non-greasy formula is infused with advanced UV filters, Vitamin E. andaloe vera to protect against sun damage and nourish the skin.

WARNINGS

For external use only.

DO NOT USE

Avoid contact with eyes; rinse thoroughlyif contact occurs.

Stop use to broken orirritated skin

OTHER SAFETY INFORMATION

Protect this product from excessive heat and direct sun. Limiting sunexposure , wearing protective clothing and using sunscreens mayreduce the risk of skin aging, skin cancer and other harmful effects ofthe sun.

Keep out of reach of children. If product is swallowed, get medical help or contact a Poison Control Center right away.

INACTIVE INGREDIENT

Water, Glycerin, Butylene Glycol, lsohexadecane, C12-15 AlkylBenzoate, Propylene Glycol Laurate, PhenylTrimethicone,Polysilicone-15,Diethylamino Hydroxybenzoyl Hexyl Benzoate.Hydrogenated Polydecene, Polyglyceryl-3 MethylglucoseDistearate,Potassium Cetyl phosphate, Cetearyl Alcohol.EthylhexylTriazone, Lauric/Myristic/Palmitic/Stearic GlyceridesPentylene Glycol,Tribehenin,Glyceryl Stearate,1.2-Hexanediol.Decyl Glucoside, Propanediol, Acrylates/C10-30 Alkyl AcrylateCrosspolymer, Arginine, Disodium Edta, PentaerythritylTetra-Di-f-Butyl Hydroxyhydrocinnamate, Sodium HyaluronateCaprylhydroxamic Acid, Propylene Glycol, Ethylhexylglycerin,Xanthan Gum

DOSAGE AND ADMINISTRATION

Reapplyevery 2 hours when exposed to sunlight.

QUESTIONS

www.myabsolutskin.com